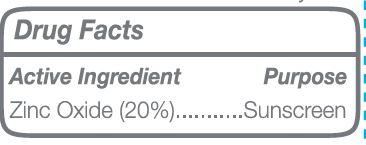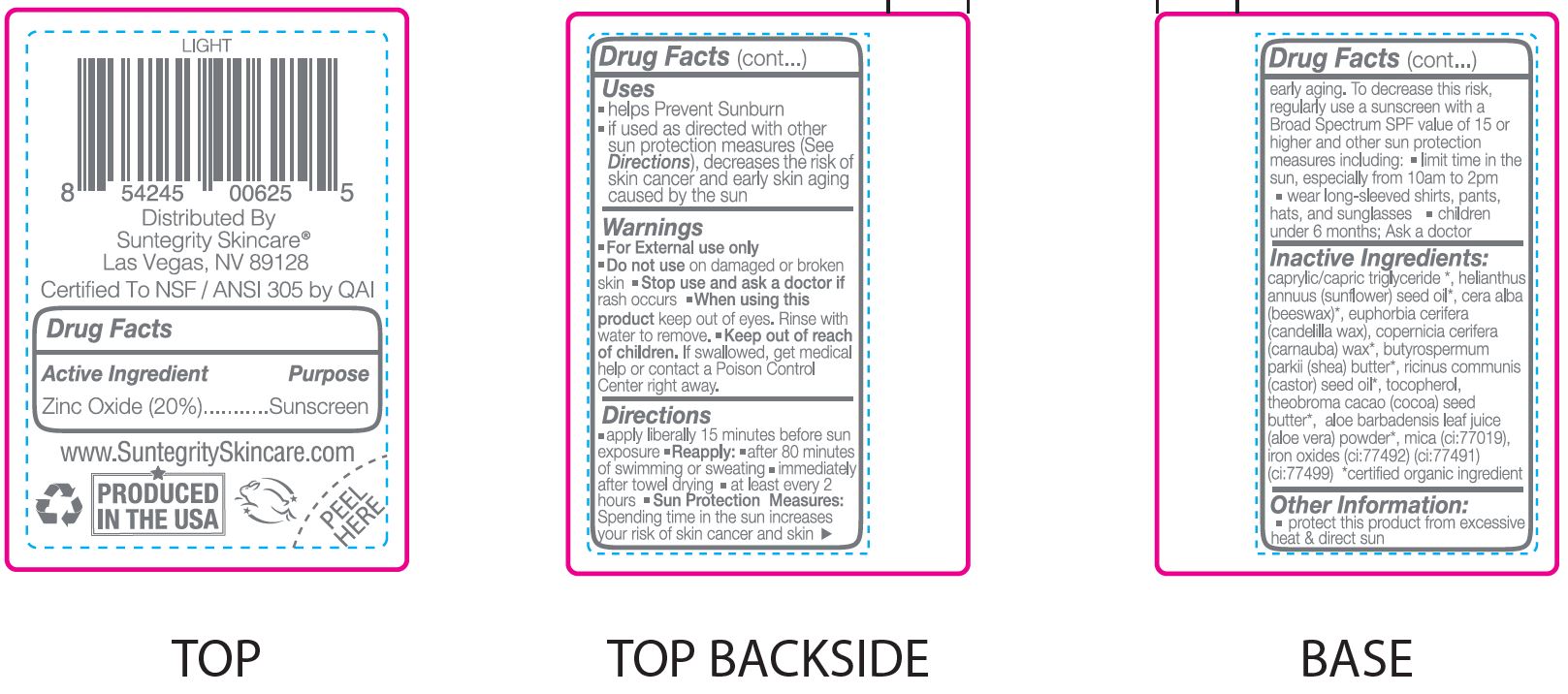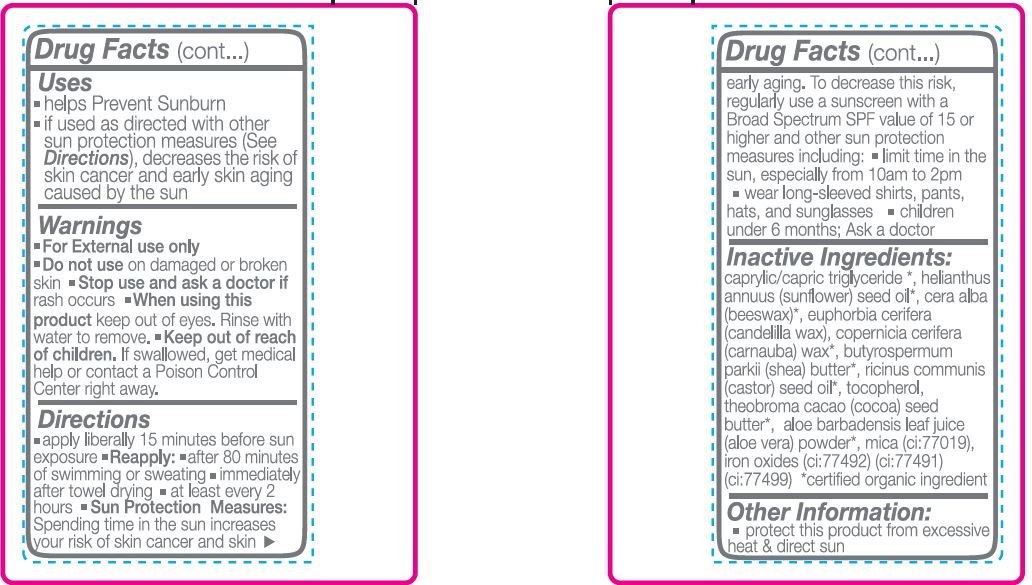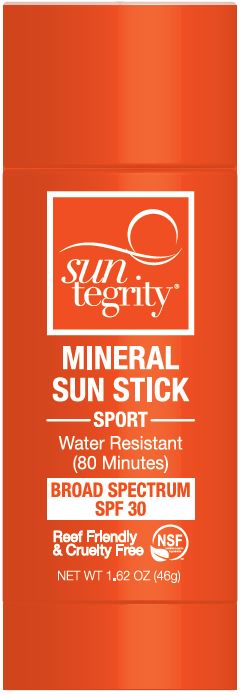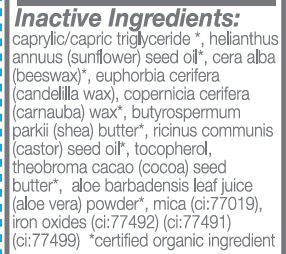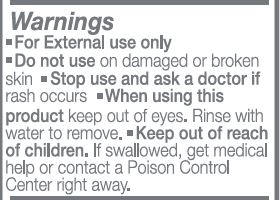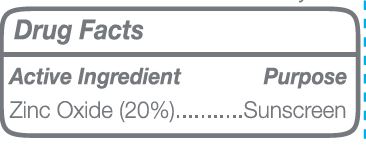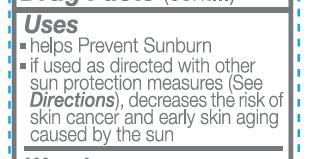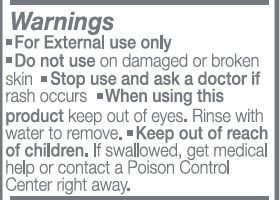 DRUG LABEL: Sunscreen
NDC: 62932-219 | Form: STICK
Manufacturer: Private Label Select Ltd CO
Category: otc | Type: HUMAN OTC DRUG LABEL
Date: 20200716

ACTIVE INGREDIENTS: ZINC OXIDE 20 g/100 g
INACTIVE INGREDIENTS: COCOA BUTTER; CASTOR OIL; ALOE VERA LEAF; .DELTA.-TOCOPHEROL; FERRIC OXYHYDROXIDE; FERROSOFERRIC OXIDE; MEDIUM-CHAIN TRIGLYCERIDES; CANDELILLA WAX; CARNAUBA WAX; MICA; FERRIC OXIDE RED; WHITE WAX; SUNFLOWER OIL; SHEA BUTTER; .ALPHA.-TOCOPHEROL, D-; .GAMMA.-TOCOPHEROL; .BETA.-TOCOPHEROL

Suntegrity, Mineral Sun Stick, SPF 30 - Tinted Light